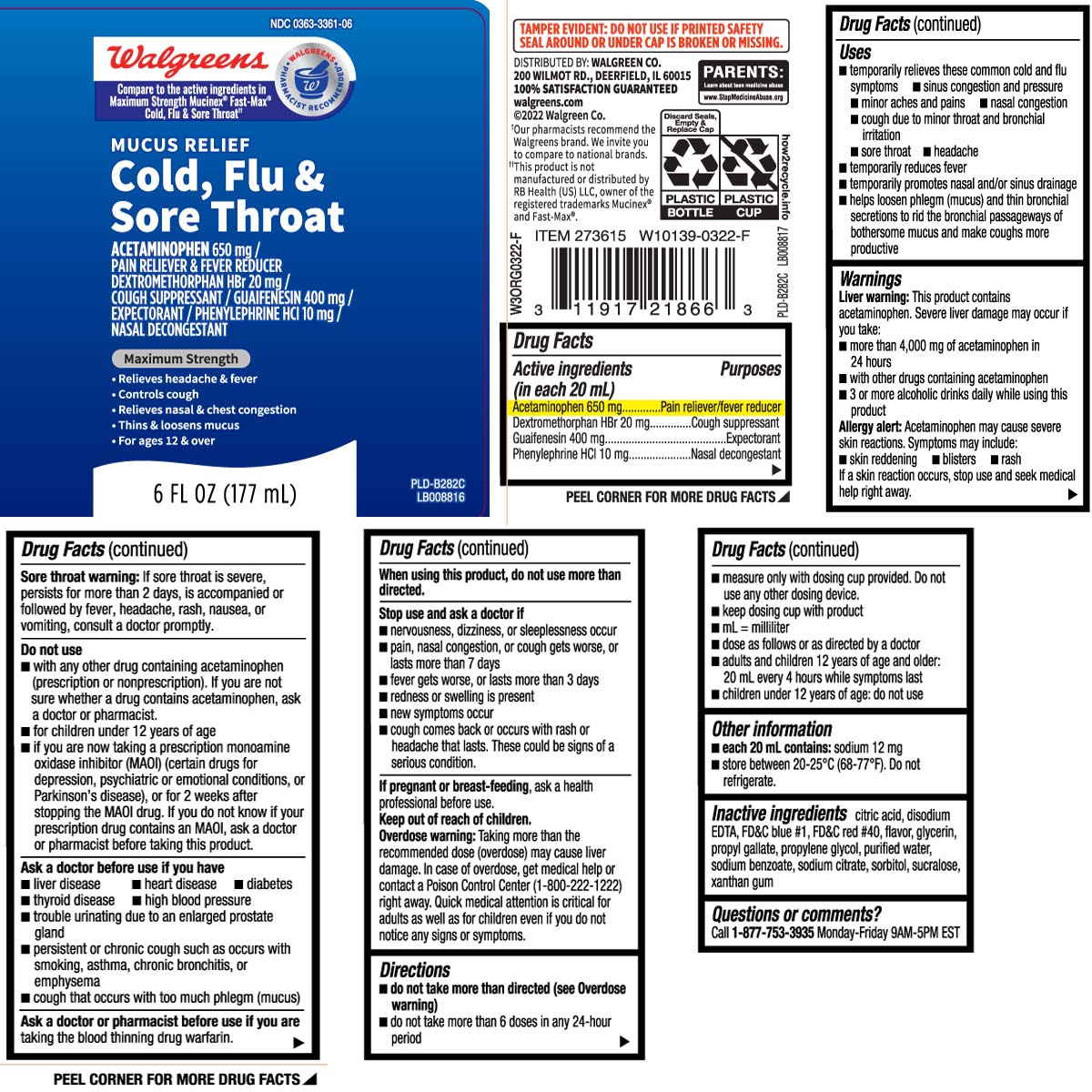 DRUG LABEL: Mucus Relief Cold Flu Sore Throat
NDC: 0363-3361 | Form: LIQUID
Manufacturer: Walgreens
Category: otc | Type: HUMAN OTC DRUG LABEL
Date: 20240716

ACTIVE INGREDIENTS: DEXTROMETHORPHAN HYDROBROMIDE 20 mg/20 mL; ACETAMINOPHEN 650 mg/20 mL; GUAIFENESIN 400 mg/20 mL; PHENYLEPHRINE HYDROCHLORIDE 10 mg/20 mL
INACTIVE INGREDIENTS: ANHYDROUS CITRIC ACID; EDETATE DISODIUM; FD&C BLUE NO. 1; FD&C RED NO. 40; GLYCERIN; PROPYL GALLATE; PROPYLENE GLYCOL; WATER; SODIUM BENZOATE; TRISODIUM CITRATE DIHYDRATE; SORBITOL; SUCRALOSE; XANTHAN GUM

Drug Facts

Active ingredients (in each 20 mL)

Acetaminophen 650 mg

Dextromethorphan HBr 20 mg

Guaifenesin 400 mg

Phenylephrine HCl 10 mg

Purposes

Pain reliever/fever reducer

Cough suppressant

Expectorant

Nasal decongestant

Uses

- temporarily relieves these common cold and flu symptoms:
  - sinus congestion and pressure
  - minor aches and pains
  - nasal congestion
  - cough due to minor throat and bronchial irritation
  - sore throat
  - headache
- temporarily reduces fever
- temporarily promotes nasal and/or sinus drainage
- helps loosen phlegm (mucus) and thin bronchial secretions to rid the bronchial passageways of bothersome mucus and make coughs more productive

Warnings

Liver warnings: This product contains acetaminophen. Severe liver damage may occur if you take:

- more than 4,000 mg of acetaminophen in 24 hours
- with other drugs containing acetaminophen
- 3 or more alcoholic drinks daily while using this product

Allergy alert: Acetaminophen may cause severe skin reactions. Symptoms may include:

- skin reddening
- blisters
- rash

If a skin reaction occurs, stop use and seek medical help right away.

Sore throat warning: If sore throat is severe, persists for more than 2 days, is accompanied or followed by fever, headache, rash, nausea or vomiting, consult a doctor promptly.

Do not use

- with any other drug containing acetaminophen (prescription or nonprescription). If you are not sure whether a drug contains acetaminophen, ask a doctor or pharmacist.
- for children under 12 years of age
- if you are now taking a prescription monoamine oxidase inhibitor (MAOI) (certain drugs for depression, psychiatric or emotional conditions, or Parkinson's disease), or for 2 weeks after stopping the MAOI drug. If you do not know if your prescription drug contains an MAOI, ask a doctor or pharmacist before taking this product.

Ask a doctor before use if you have

- liver disease
- heart disease
- diabetes
- thyroid disease
- high blood pressure
- persistent or chronic cough such as occurs with smoking, asthma, chronic bronchitis or emphysema
- cough that occurs with too much phlegm (mucus)
- trouble urinating due to an enlarged prostate gland

Ask a doctor or pharmacist before use if you are

taking the blood thinning drug warfarin

When using this product,

do not use more than directed.

Stop use and ask a doctor if

- nervousness, dizziness or sleeplessness occur
- pain, nasal congestion or cough gets worse or lasts more than 7 days
- fever gets worse or lasts more than 3 days
- redness or swelling is present
- new symptoms occur
- cough comes back, or occurs with rash or headache that lasts.

These could be signs of a serious condition.

If pregnant or breast-feeding,

ask a health professional before use.

Keep out of reach of children.

Overdose warning: Taking more than the recommended dose (overdose) may cause liver damage. In case of overdose, get medical help or contact a Poison Control Center (1-800-222-1222) right away. Quick medical attention is critical for adults as well as for children even if you do not notice any signs or symptoms.

Directions

- do not take more than directed (see overdose warning)
- do not take more than 6 doses in any 24-hour period
- measue only with dosing cup provided. Do not use any other dosing device.
- keep dosing cup with product
- mL = milliliter
- dose as follows or as directed by a doctor
- adults and children 12 years of age and older: 20 mL every 4 hours while symptoms last
- children under 12 years of age: do not use

Other information

- each 20 mL contains: sodium 12 mg
- store between 20-25ºC (68-77ºF). Do not refrigerate.

Inactive ingredients

anhydrous citric acid, disodium EDTA,, FD&C blue #1, FD&C red #40, flavor, glycerin, propyl gallate, propylene glycol, purified water, sodium benzoate, sodium citrate, sorbitol, sucralose, xanthan gum

Questions or comments?

Call 1-877-753-3935 Monday-Friday 9AM-5PM EST

Principal Display Panel

Compare to the active ingredient in Maximum Strength Mucinex® Fast-Max® Cold, Flu, & Sore Throat††

MUCUS RELIEF

Cold, Flu & Sore Throat

ACETAMINOPHEN 650 mg /

PAIN RELIEVER & FEVER REDUCER

DEXTROMETHORPHAN HBr 20 mg /

COUGH SUPPRESSANT

GUAIFENESIN 400 mg /

EXPECTORANT

PHENYLEPHRINE HCI 10 mg /

NASAL DECONGESTANT

Maximum Strength

- Relieves headache,fever, sore throat, nasal & chest congestion
- Controls cough
- Relieves nasal & chest congestion
- Thins & loosens mucus
- For ages 12 & over

FL OZ (mL)

††This product is not manufactured or distributed by RB Health [US] LLC owner of registered trademarks Mucinex® Fast-Max®

TAMPER EVIDENT: DO NOT USE IF PRINTED SAFETY SEAL AROUND OR UNDER CAP IS BROKEN OR MISSING.

DISTRIBUTED BY: WALGREEN CO.

200 WILMOT RD. DEERFIELD, IL 60015

walgreens.com

Package Label

WALGREENS Mucus Relief Cold, Flu & Sore Throat